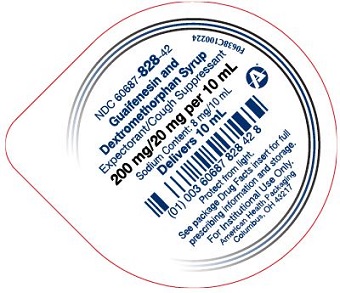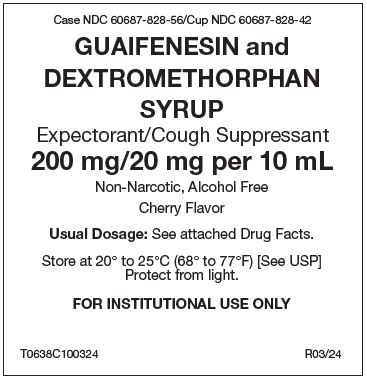 DRUG LABEL: Guaifenesin DM
NDC: 60687-828 | Form: SYRUP
Manufacturer: American Health Packaging
Category: otc | Type: HUMAN OTC DRUG LABEL
Date: 20240804

ACTIVE INGREDIENTS: GUAIFENESIN 200 mg/10 mL; DEXTROMETHORPHAN 20 mg/10 mL
INACTIVE INGREDIENTS: ANHYDROUS CITRIC ACID; FD&C RED NO. 40; GLYCERIN; MENTHOL, UNSPECIFIED FORM; WATER; SODIUM BENZOATE; SODIUM CITRATE, UNSPECIFIED FORM; SACCHARIN SODIUM; SUCROSE

GUAIFENESIN and DEXTROMETHORPHAN SYRUP
Drug Facts

Active ingredient (in each 10 mL Cup)

Guaifenesin 200 mg
Dextromethorphan Hydrobromide 20 mg

Purpose

Expectorant
Cough Suppressant

Uses

- helps loosen phlegm (mucus) and thin bronchial secretions to make coughs more productive
- temporarily relieves cough due to minor throat and bronchial irritation as may occur with a cold

Warnings

Do not use if you are now taking a prescription monoamine oxidase inhibitor (MAOI) (certain drugs for depression, psychiatric, or emotional conditions, or Parkinson's disease), or for 2 weeks after stopping the MAOI drug. If you do not know if your prescription drug contains an MAOI, ask a doctor or pharmacist before taking this product.

Ask a doctor before use if you have

- cough that occurs with too much phlegm (mucus)
- cough that lasts or is chronic such as occurs with smoking, asthma, chronic bronchitis, or emphysema

Stop use and ask a doctor if

- cough lasts more than 7 days, comes back, or is accompanied by fever, rash, or persistent headache. These could be signs of a serious condition.
- you are hypersensitive to any of the ingredients.

If pregnant or breast-feeding,

ask a health professional before use.

Keep out of reach of children.

In case of overdose, get medical help or contact a Poison Control Center right away.

Directions

Follow dosage below or use as directed by a physician.

- do not take more than 6 doses in any 24-hour period.

Age (yr) | Dose (mL)
adults and children 12 years and over | 10 mL (2 teaspoonfuls) every 4 hours
children 6 years to under 12 years | 5 mL (1 teaspoonful) every 4 hours
children 2 years to under 6 years | 2.5 mL (1/2 teaspoonful) every 4 hours
children under 2 years | ask a doctor

Other Information

- Each 10 mL contains: sodium 8 mg
- Store at controlled room temperature between 20° to 25°C (68° to 77°F) [see USP]. Protect from light.
- DO NOT USE IF SEAL IS BROKEN.
- Guaifenesin Syrup and Dextromethorphan is a red, cherry flavored syrup and is available in the following dosage forms:
  5 mL unit-dose cups: 100 cups (10 x 10) NDC 60687-817-17
  10 mL unit-dose cups: 100 cups (10 x 10) NDC 60687-828-56

Inactive Ingredients

citric acid, FD&C Red No. 40, flavoring, glycerin, menthol, purified water, sodium benzoate, sodium citrate, sodium saccharin, and sucrose.

Questions or comments?

Call 1-800-845-8210

Professional Note: Guaifenesin has been shown to produce a color interference with certain clinical laboratory determinations of 5-hydroxyindoleacetic acid (5-HIAA) and vanillylmandelic acid (VMA).

Distributed by:
American Health Packaging
Columbus, OH 43217

R0324

Package/Label Principal Display Panel - Label

Case NDC 60687-828-56/Cup NDC 60687-828-42

GUAIFENESIN and
DEXTROMETHORPHAN
SYRUP

Expectorant/Cough Suppressant

200 mg/20 mg per 10 mL

Non-Narcotic, Alcohol Free
Cherry Flavor

Usual Dosage: See attached Drug Facts.

Store at 20° to 25°C (68° to 77°F) [See USP]
Protect from light.

FOR INSTITUTIONAL USE ONLY

T0638C100324 R03/24

Package/Label Principal Display Panel – Cup Lid – 200 mg/20 mg per 10 mL

NDC 60687- 828-42

Guaifenesin and
Dextromethorphan Syrup

Expectorant/cough Suppressant

200 mg/20 mg per 10 mL

Sodium Content: 8 mg/10 mL

Delivers 10 mL

Protect from light

See package Drug Facts insert for full
prescribing information and storage

For Institutional Use Only.

American Health Packaging
Columbus, OH 43217

F0638C100224